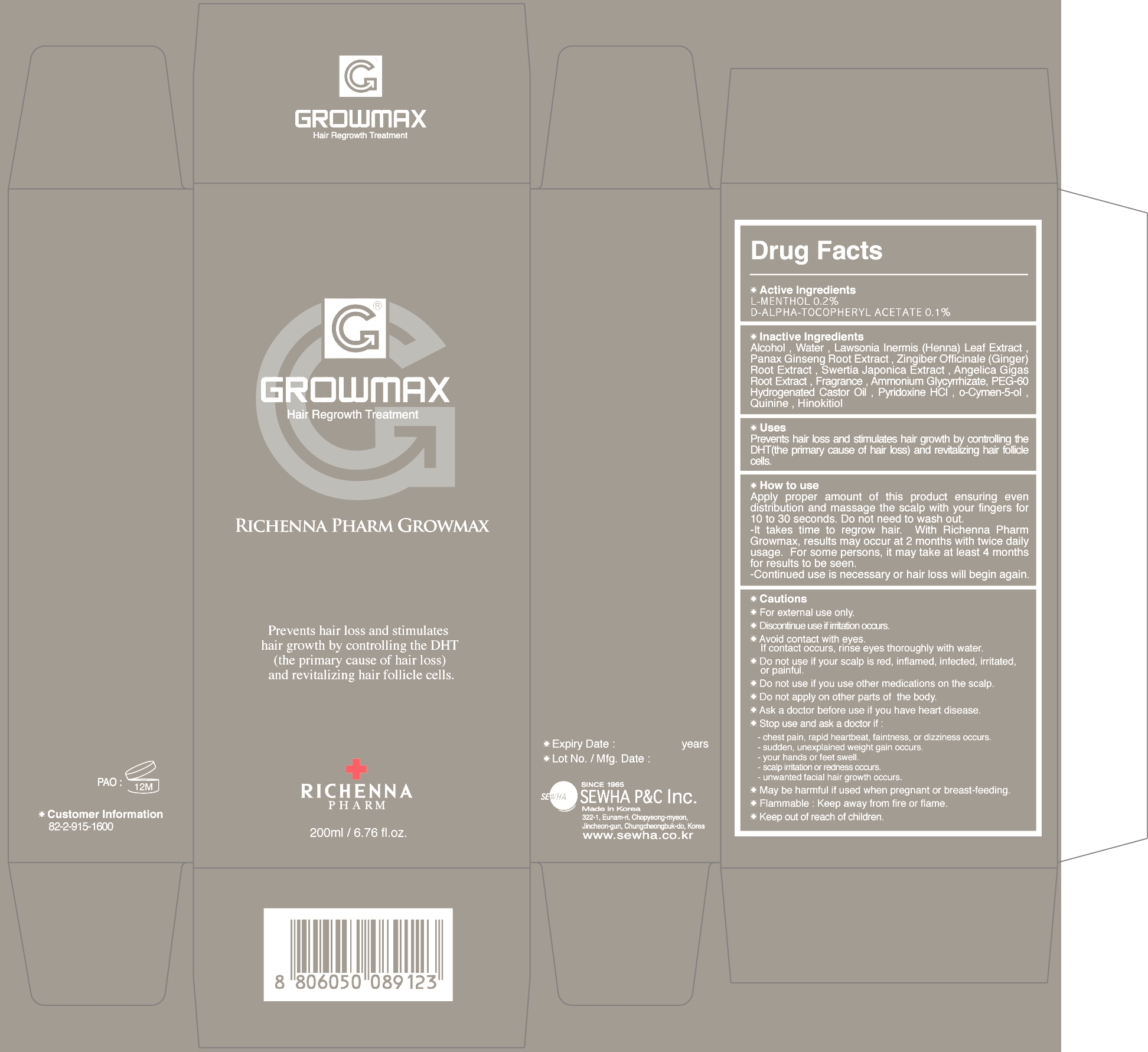 DRUG LABEL: RICHENNAPHARM
NDC: 50629-1005 | Form: LIQUID
Manufacturer: SEWHA P&C INC
Category: otc | Type: HUMAN OTC DRUG LABEL
Date: 20100428

ACTIVE INGREDIENTS: LEVOMENTHOL 0.4 mL/200 mL; ALPHA-TOCOPHEROL ACETATE 0.2 mL/200 mL
INACTIVE INGREDIENTS: LAWSONIA INERMIS LEAF

RICHENNAPHARMGROWMAX Hair care Tonic

Drug Facts

Active ingredients :

L-MENTHOL 0.2%
D-ALPHA-TOCOPHERYL ACETATE 0.1%
How to use
- Apply proper amount of this product ensuring even distribution and massage the scalp with your fingers for 10 to 30 seconds. Do not need to wash out.
- Provides an excellent tonic effect and prevents depilation(hair-loss). For some persons, it may take at least 4 months for result to be seen.
- Continued use is necessary or hair loss will begin again.

Cautions
-For external use only.
-Discontinue use if irritation occurs.
-Avoid contact with eyes. If contact occurs, rinse eyes throughly with water.
-Flammable: Keep away from fire or flame.
-Keep out of reach of children.
Do not use
-Do not use if your scalp is red, inflamed, infected, irritated, or painful.
-Do not use if you use other medications on the scalp.
-Do not apply on other parts of the body.
Ask a doctor before use if you have heart disease.
-Stop use and ask a doctor if :
-hest pain, rapid heartbeat, faintness, or dizziness occurs.
-sudden, unexplained weight gain occurs.
-your hands or feet swell.
-scalp irritation or redness occurs.
-unwanted facial hair growth occurs.
-May be harmful if used when pregnant or breast-feeding.

RICHENNAPHARMGROWMAX Hair care Tonic

RICHENNA PHARM
200ml/ 6.76 fl.oz